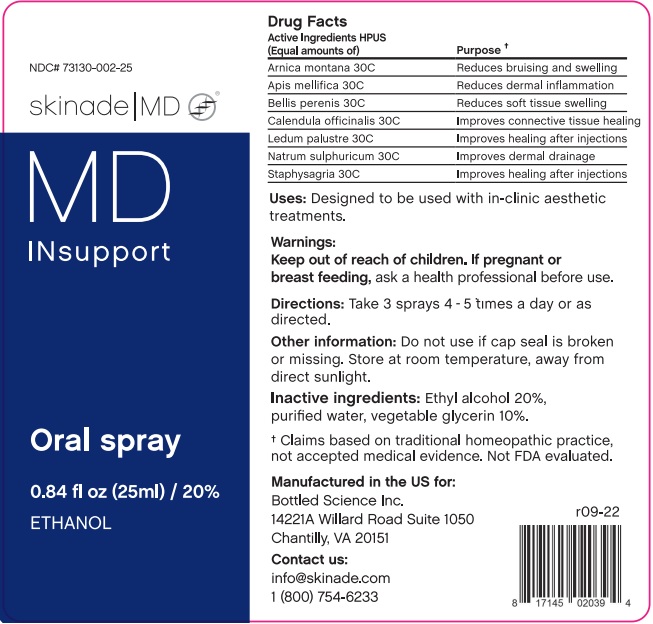 DRUG LABEL: Skinade MD INsupport
NDC: 73130-002 | Form: SPRAY
Manufacturer: Bottled Science, Inc.
Category: homeopathic | Type: HUMAN OTC DRUG LABEL
Date: 20221210

ACTIVE INGREDIENTS: APIS MELLIFERA 30 [hp_C]/25 mL; ARNICA MONTANA WHOLE 30 [hp_C]/25 mL; BELLIS PERENNIS WHOLE 30 [hp_C]/25 mL; CALENDULA OFFICINALIS FLOWER 30 [hp_C]/25 mL; LEDUM PALUSTRE WHOLE 30 [hp_C]/25 mL; SODIUM SULFATE 30 [hp_C]/25 mL; DELPHINIUM STAPHISAGRIA SEED 30 [hp_C]/25 mL
INACTIVE INGREDIENTS: ALCOHOL; WATER; GLYCERIN

MD INsupport

Drug Facts

Active Ingredients HPUS

(Equal amounts of)

Arnica montana 30C Reduces bruising and swelling

Apis mellifica 30C Reduces dermal inflammation

Bellis perenis 30C Reduces soft tissue swelling

Calendula officinalis 30C Improves connective tissue healing

Ledum palustre 30C Improves healing after injections

Natrum sulphuricum 30C Improves dermal drainage

Staphysagria 30C Improves healing after injections

✝ Claims based on traditional homeopathic practive, not accepted medical evidence. Not FDA evaluated.

INDICATIONS AND USAGE

Uses: Designed to be used with in-clinic aesthetic treatments.

WARNINGS

Warnings: If pregnant or breast feeding, ask a health professional before use.

Keep out of reach of children.

DOSAGE AND ADMINISTRATION

Directions: Take 3 sprays 4-5 times a day or as directed.

Other information: Do not use if cap seal is broken or missing. Store at room temperature, away from direct sunlight.

INACTIVE INGREDIENT

Inactive ingredients: Ethyl alcohol 20%, purified water, vegetable glycerin 10%.

QUESTIONS

Manufactured in the US for:

Bottled Science Inc.

14221A Willard Road Suite 1050

Chantilly, VA 20151

Contact us:

info@skinade.com

1 (800) 754-6233

PACKAGE LABEL

NDC# 73130-002-25

skinade MD

MD

INsupport

Oral spray

0.84 fl oz (25ml) / 20%

ETHANOL

PURPOSE

Designed to be used with in-clinic aesthetic treatments.